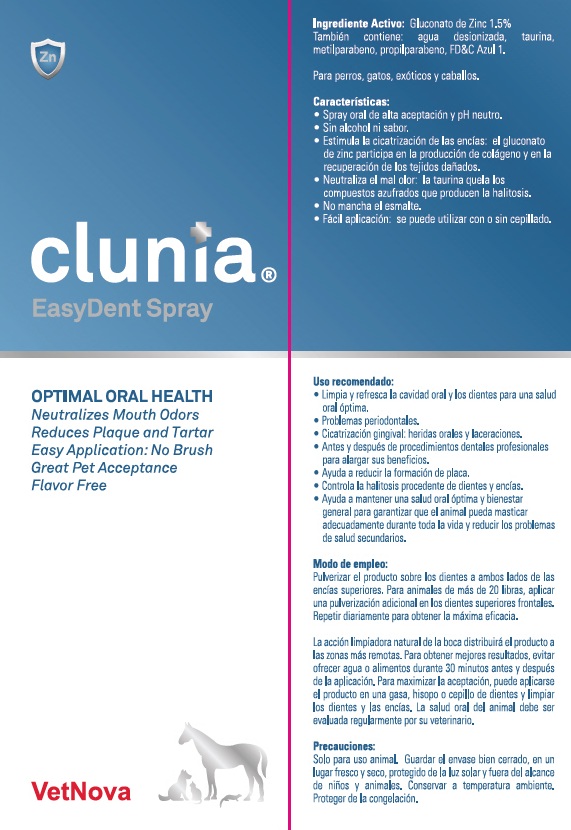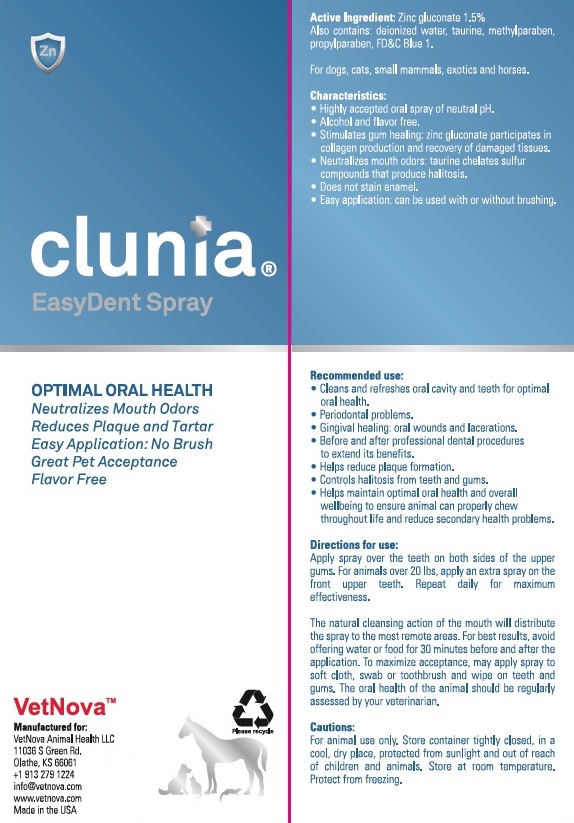 DRUG LABEL: Clunia EasyDent
NDC: 86145-400 | Form: LIQUID
Manufacturer: Vetnova Animal Health LLC
Category: animal | Type: OTC ANIMAL DRUG LABEL
Date: 20251118

ACTIVE INGREDIENTS: zinc gluconate 15 mg/1 mL
INACTIVE INGREDIENTS: LYSINE; taurine; WATER; Methylparaben; Propylparaben

Clunia® EasyDent Spray

Active Ingredient: Zinc gluconate 1.5%

Also contains deionized water, taurine, methylparaben, propylparaben, FD&C Blue 1.

For use in dogs, cats, small mammals, exotics and horses.

Characteristics:

- Highly accepted oral spray of neutral pH.
- Alcohol and flavor free.
- Stimulates gum healing: zinc gluconate participates in collagen production and recovery of damaged tissues.
- Neutralizes mouth odors: taurine chelates sulfur compounds that produce halitosis.
- Does not stain enamel.
- Easy application: can be used with or without brushing.

VETERINARY INDICATIONS

Recommended use:

- Cleans and refreshes oral cavity and teeth for optimal oral health.
- Periodontal problems.
- Gingival healing: oral wounds and lacerations.
- Before and after professional dental procedures to extend its benefits.
- Helps reduce plaque formation.
- Controls halitosis from teeth and gums.
- Helps maintain optimal oral health and overall wellbeing to ensure animal can properly chew throughout life and reduce secondary health problems.

DOSAGE AND ADMINISTRATION

Directions for use:

Apply spray over the teeth on both sides of the upper gums. For animals over 20 lbs, apply an extra spray on the from upper teeth. Repeat dairy for maximum effectiveness For best result, repeat daily and avoid offering water or food for 30 minutes before and after application.

The natural cleansing action of the mouth will distribute the spray to the most remote areas. For best results, avoid offering water or food for 30 minutes before and after the application. To maximize acceptance, may apply spray to soft cloth, swab or toothbrush and wipe on teeth and gums. The oral health of the animal should be regularly assessed by your veterinarian.

PRECAUTIONS

Cautions:

For animal use only. Store container tightly closed, in a cool, dry place, protected from sunlight and out of reach of children and animals. Store at room temperature. Protect from freezing.

Manufactured for:
VetNova Animal Health LLC
11036 S Green Rd.
Olathe, KS 66061
+1 913 279 1224
info@vetnova.com
www.vetnova.com
Made in USA

1032.1222

Please recycle

PRINCIPAL DISPLAY PANEL - 59 ml Bottle Box

clunia®
EasyDent Spray

OPTIMAL ORAL HEALTH

Neutralizes Mouth Odors
Reduces Plaque and Tartar
Easy Application: No Brush
Great Pet Acceptance
Flavor Free